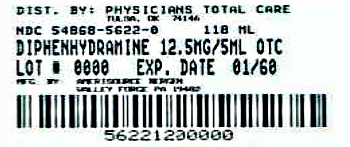 DRUG LABEL: Diphenhydramine Hydrochloride
NDC: 54868-5622 | Form: LIQUID
Manufacturer: Physicians Total Care, Inc.
Category: otc | Type: HUMAN OTC DRUG LABEL
Date: 20120605

ACTIVE INGREDIENTS: DIPHENHYDRAMINE HYDROCHLORIDE 12.5 mg/5 mL
INACTIVE INGREDIENTS: CITRIC ACID MONOHYDRATE; D&C RED NO. 33; FD&C RED NO. 40; GLYCERIN; HIGH FRUCTOSE CORN SYRUP; POLOXAMER 407; WATER; SODIUM BENZOATE; SODIUM CHLORIDE; SODIUM CITRATE; SORBITOL

Active ingredient (in each 5 mL teaspoonful)

Diphenhydramine HCl 12.5 mg

Purpose

Antihistamine

Uses

- temporarily relieves these symptoms due to hay fever or other upper respiratory allergies:
- sneezing
- itching of the nose or throat
- runny nose
- itchy, watery eyes
- temporarily relieves these symptoms due to the common cold:
- sneezing
- runny nose

Warnings

Do not use

- with any other product containing diphenhydramine, even one used on skin
- to make a child sleepy

Ask a doctor before use if you have

- a breathing problem such as emphysema or chronic bronchitis
- glaucoma
- trouble urinating due to an enlarged prostate gland
- a sodium-restricted diet

Ask a doctor or pharmacist before use if you are

taking sedatives or tranquilizers

When using this product

- avoid alcoholic drinks
- marked drowsiness may occur
- excitability may occur, especially in children
- alcohol, sedatives and tranquilizers may increase drowsiness
- be careful when driving a motor vehicle or operating machinery

If pregnant or breast-feeding,

ask a health professional before use.

Keep out of reach of children.

In case of overdose, get medical help or contact a Poison Control Center right away.

Directions

- if needed, take every 4-6 hours
- do not take more than 6 doses in 24 hours

children under 4; years of age | do not use
children 4 to under 6; years of age | do not use unless directed by a doctor
children 6 to under; 12 years of age | 1 to 2 teaspoonfuls; (12.5 mg to 25 mg)
adults and children; 12 years of age; and over | 2 to 4 teaspoonfuls; (25 mg to 50 mg)

Other information

- each teaspoonful contains: sodium 15 mg
- store at 20°-25°C (68°-77°F)

Inactive ingredients

citric acid, D&C red no. 33, FD&C red no. 40, flavor, glycerin, high fructose corn syrup, poloxamer 407, purified water, sodium benzoate, sodium chloride, sodium citrate, sorbitol

Questions or comments?

1-800-719-9260

Principal Display Panel

Diphenhydramine Hydrochloride

12.5 mg/ 5 mL

NDC 54868-5622-0

Relieves:

Sneezing

Itchy, Watery Eyes

Runny Nose

Itchy Throat

See New Warning and Dosing Directions

Cherry Flavored

4 fl oz (118 mL)

Alcohol Free

Additional barcode labeling by:
Physicians Total Care, Inc.
Tulsa, Oklahoma 74146